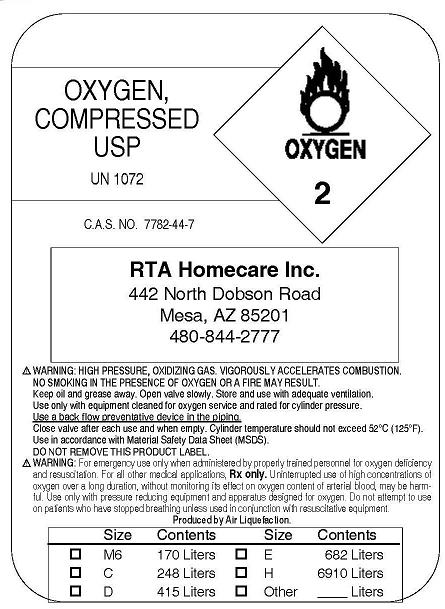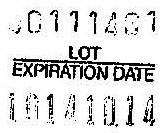 DRUG LABEL: Oxygen
NDC: 54982-0001 | Form: GAS
Manufacturer: RTA Homecare, Inc.
Category: prescription | Type: HUMAN PRESCRIPTION DRUG LABEL
Date: 20091029

ACTIVE INGREDIENTS: Oxygen 99 L/100 L

Oxygen